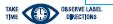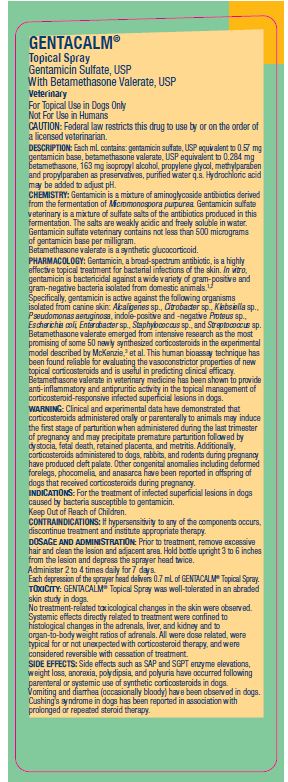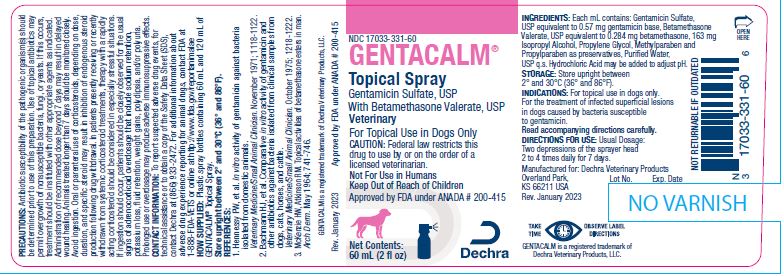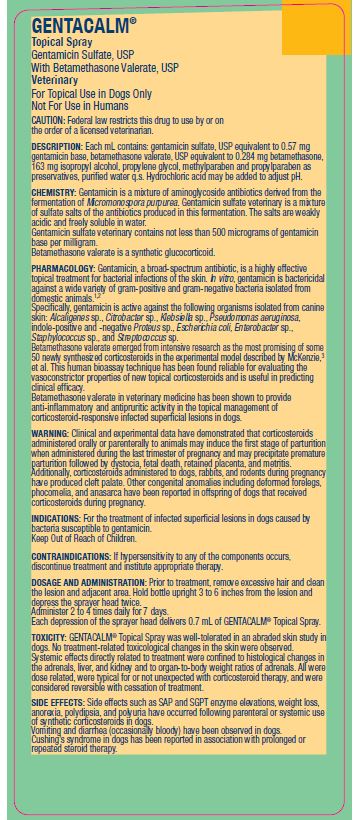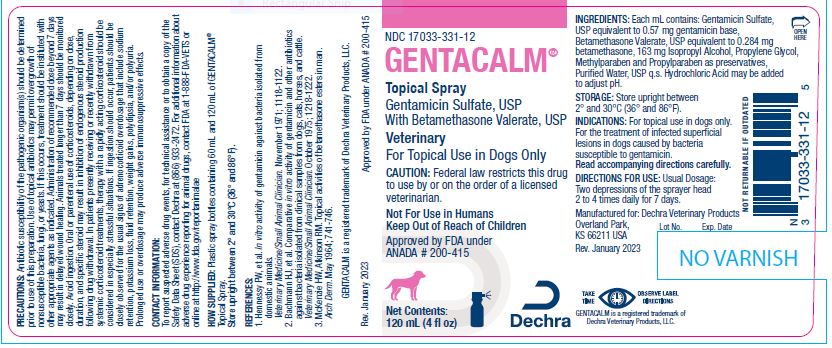 DRUG LABEL: GENTACALM
NDC: 17033-331 | Form: SPRAY, METERED
Manufacturer: Dechra Veterinary Products
Category: animal | Type: PRESCRIPTION ANIMAL DRUG LABEL
Date: 20240307

ACTIVE INGREDIENTS: GENTAMICIN SULFATE 0.57 mg/1 mL; BETAMETHASONE VALERATE 0.284 mg/1 mL

GENTACALM® Topical Spray

VETERINARY INDICATIONS

Gentamicin Sulfate, USP With Betamethasone Valerate, USP

Veterinary
For Topical Use in Dogs Only

CAUTION:

Federal law restricts this drug to use by or on the order of a licensed veterinarian.

Not For Use in Humans
Keep Out of Reach of Children

Approved by FDA under ANADA # 200-415

INGREDIENTS:

Each mL contains: Gentamicin Sulfate, USP equivalent to 0.57 mg gentamicin base, Betamethasone Valerate, USP equivalent to 0.284 mg betamethasone, 163 mg Isopropyl Alcohol, Propylene Glycol, Methylparaben and Propylparaben as preservatives, Purified Water, USP q.s. Hydrochloric Acid may be added to adjust pH.

STORAGE:

Store upright between 2° and 30°C (36° and 86°F).

INDICATIONS:

For topical use in dogs only. For the treatment of infected superficial lesions in dogs caused by bacteria susceptible to gentamicin.
Read accompanying directions carefully.

DIRECTIONS FOR USE:

Usual Dosage: Two depressions of the sprayer head 2 to 4 times daily for 7 days.

INFORMATION FOR OWNERS/CAREGIVERS

Manufactured for: Dechra Veterinary Products
Overland Park,
KS 66211 USA
Rev. January 2023

GENTACALM is a registered trademark of Dechra Veterinary Products, LLC.

DESCRIPTION:

Each mL contains: gentamicin sulfate, USP equivalent to 0.57 mg gentamicin base, betamethasone valerate, USP equivalent to 0.284 mg betamethasone, 163 mg isopropyl alcohol, propylene glycol, methylparaben and propylparaben as preservatives, purified water q.s. Hydrochloric acid may be added to adjust pH.

CHEMISTRY:

Gentamicin is a mixture of aminoglycoside antibiotics derived from the fermentation of Micromonospora purpurea. Gentamicin sulfate veterinary is a mixture of sulfate salts of the antibiotics produced in this fermentation. The salts are weakly acidic and freely soluble in water.
Gentamicin sulfate veterinary contains not less than 500 micrograms of gentamicin base per milligram.
Betamethasone valerate is a synthetic glucocorticoid.

PHARMACOLOGY:

Gentamicin, a broad-spectrum antibiotic, is a highly effective topical treatment for bacterial infections of the skin. In vitro, gentamicin is bactericidal against a wide variety of gram-positive and gram-negative bacteria isolated from domestic animals.^1,2
Specifically, gentamicin is active against the following organisms isolated from canine skin: Alcaligenes sp., Citrobacter sp., Klebsiella sp., Pseudomonas aeruginosa, indole-positive and -negative Proteus sp., Escherichia coli, Enterobacter sp., Staphylococcus sp., and Streptococcus sp.
Betamethasone valerate emerged from intensive research as the most promising of some 50 newly synthesized corticosteroids in the experimental model described by McKenzie,^3 et al. This human bioassay technique has been found reliable for evaluating the vasoconstrictor properties of new topical corticosteroids and is useful in predicting clinical efficacy.
Betamethasone valerate in veterinary medicine has been shown to provide anti-inflammatory and antipruritic activity in the topical management of corticosteroid-responsive infected superficial lesions in dogs.

WARNING:

Clinical and experimental data have demonstrated that corticosteroids administered orally or parenterally to animals may induce the first stage of parturition when administered during the last trimester of pregnancy and may precipitate premature parturition followed by dystocia, fetal death, retained placenta, and metritis.
Additionally, corticosteroids administered to dogs, rabbits, and rodents during pregnancy have produced cleft palate. Other congenital anomalies including deformed forelegs, phocomelia, and anasarca have been reported in offspring of dogs that received corticosteroids during pregnancy.

INDICATIONS:

For the treatment of infected superficial lesions in dogs caused by bacteria susceptible to gentamicin.
Keep Out of Reach of Children.

CONTRAINDICATIONS:

If hypersensitivity to any of the components occurs, discontinue treatment and institute appropriate therapy.

DOSAGE AND ADMINISTRATION:

Prior to treatment, remove excessive hair and clean the lesion and adjacent area. Hold bottle upright 3 to 6 inches from the lesion and
depress the sprayer head twice.
Administer 2 to 4 times daily for 7 days.
Each depression of the sprayer head delivers 0.7 mL of GENTACALM® Topical Spray.

TOXICITY:

GENTACALM® Topical Spray was well-tolerated in an abraded skin study in dogs.

No treatment-related toxicological changes in the skin were observed. Systemic effects directly related to treatment were confined to histological changes in the adrenals, liver, and kidney and to organ-to-body weight ratios of adrenals. All were dose related, were typical for or not unexpected with corticosteroid therapy, and were considered reversible with cessation of treatment.

Systemic effects directly related to treatment were confined to histological changes in the adrenals, liver, and kidney and to organ-to-body weight ratios of adrenals. All were dose related, were typical for or not unexpected with corticosteroid therapy, and were considered reversible with cessation of treatment

SIDE EFFECTS:

Side effects such as SAP and SGPT enzyme elevations, weight loss, anorexia, polydipsia, and polyuria have occurred following parenteral or systemic use of synthetic corticosteroids in dogs.
Vomiting and diarrhea (occasionally bloody) have been observed in dogs. Cushing’s syndrome in dogs has been reported in association with prolonged or repeated steroid therapy.

PRECAUTIONS:

Antibiotic susceptibility of the pathogenic organism(s) should be determined prior to use of this preparation.
Use of topical antibiotics may permit overgrowth of nonsusceptible bacteria, fungi, or yeasts.
If this occurs, treatment should be instituted with other appropriate agents as indicated.
Administration of recommended dose beyond 7 days may result in delayed wound healing.
Animals treated longer than 7 days should be monitored closely.
Avoid ingestion. Oral or parenteral use of corticosteroids, depending on dose, duration, and specific steroid may result in inhibition of endogenous steroid production following drug withdrawal. In patients presently receiving or recently withdrawn from systemic corticosteroid treatments, therapy with a rapidly acting corticosteroid should be considered in especially stressful situations.
If ingestion should occur, patients should be closely observed for the usual signs of adrenocorticoid overdosage that include sodium retention, potassium loss, fluid retention, weight gains, polydipsia, and/or polyuria. Prolonged use or overdosage may produce adverse immunosuppressive effects.

CONTACT INFORMATION:

To report suspected adverse drug events, for technical assistance or to obtain a copy of the Safety Data Sheet (SDS), contact Dechra at (866) 933-2472. For additional information about adverse drug experience reporting for animal drugs, contact FDA at 1-888-FDA-VETS or online at http://www.fda.gov/reportanimalae

HOW SUPPLIED:

Plastic spray bottles containing 60 mL and 120 mL of GENTACALM® Topical Spray.

STORAGE AND HANDLING

Store upright between 2° and 30°C (36° and 86°F).

REFERENCES:

1. Hennessy PW, et al. In vitro activity of gentamicin against bacteria isolated from domestic animals.
Veterinary Medicine/Small Animal Clinician. November 1971; 1118-1122.
2. Bachmann HJ, et al. Comparative in vitro activity of gentamicin and other antibiotics against bacteria isolated from clinical samples from dogs, cats, horses, and cattle.
Veterinary Medicine/Small Animal Clinician. October 1975; 1218-1222.
3. McKenzie HW, Atkinson RM. Topical activities of betamethasone esters in man.
Arch Derm. May 1964; 741-746.

INFORMATION FOR OWNERS/CAREGIVERS

GENTACALM is a registered trademark of Dechra Veterinary Products, LLC.

Rev. January 2023 Approved by FDA under ANADA # 200-415